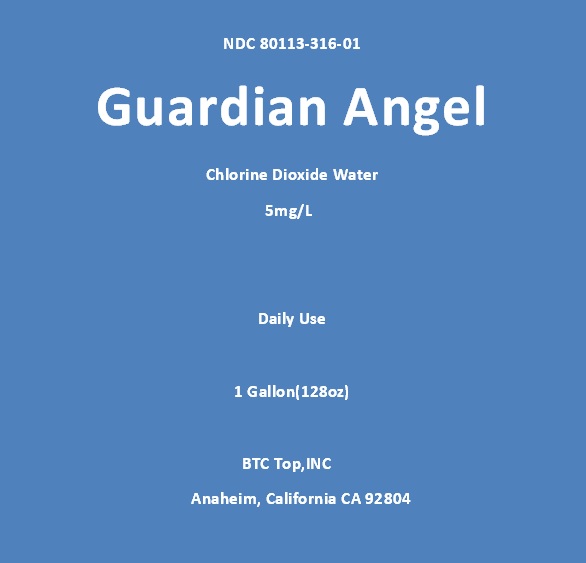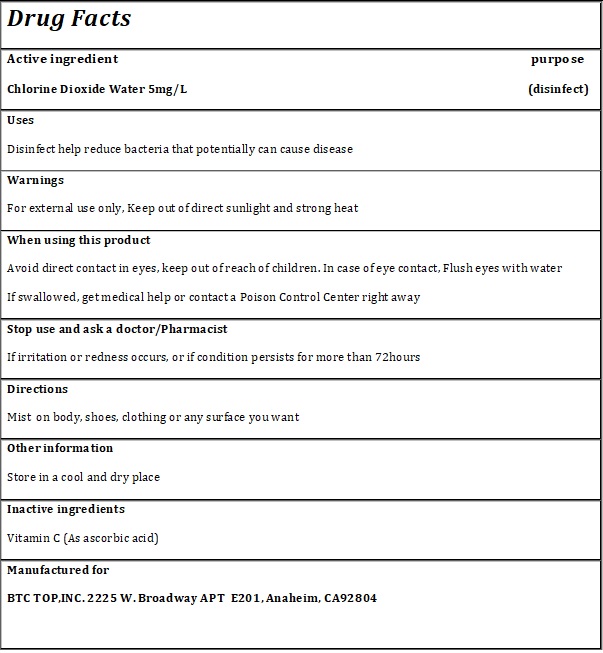 DRUG LABEL: Guardian Angel
NDC: 80113-316 | Form: LIQUID
Manufacturer: BTC TOP, INC
Category: otc | Type: HUMAN OTC DRUG LABEL
Date: 20200816

ACTIVE INGREDIENTS: CHLORINE DIOXIDE 5 mg/1 1; WATER 2 L/1 1
INACTIVE INGREDIENTS: ASCORBIC ACID 5 mg/1 1

Vitamin C (As ascorbic acid)

neutrilize ClO2 water